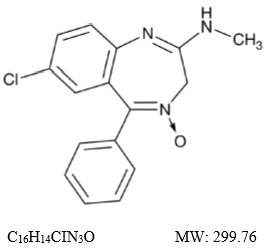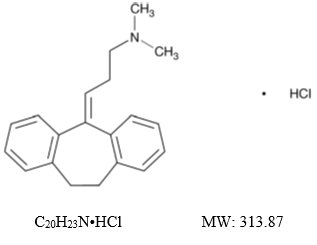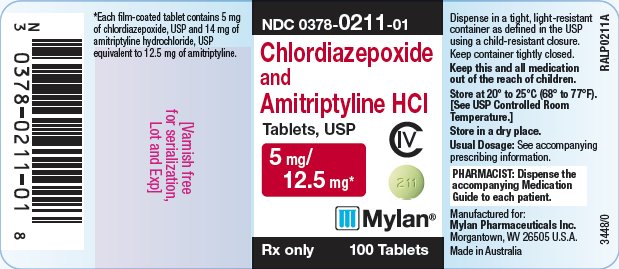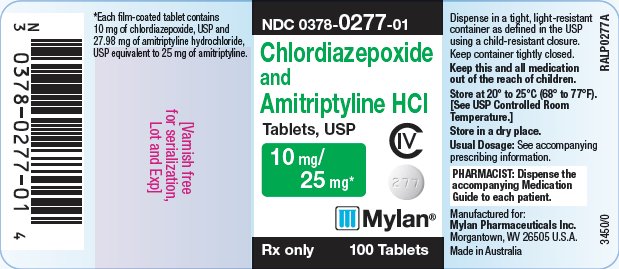 DRUG LABEL: Chlordiazepoxide and Amitriptyline Hydrochloride
NDC: 0378-0211 | Form: TABLET, FILM COATED
Manufacturer: Mylan Pharmaceuticals Inc.
Category: prescription | Type: HUMAN PRESCRIPTION DRUG LABEL
Date: 20250707
DEA Schedule: CIV

ACTIVE INGREDIENTS: CHLORDIAZEPOXIDE 5 mg/1 1; AMITRIPTYLINE HYDROCHLORIDE 14 mg/1 1
INACTIVE INGREDIENTS: SILICON DIOXIDE; CROSCARMELLOSE SODIUM; HYDROXYPROPYL CELLULOSE, UNSPECIFIED; HYPROMELLOSE, UNSPECIFIED; MAGNESIUM STEARATE; MICROCRYSTALLINE CELLULOSE; POLYETHYLENE GLYCOL, UNSPECIFIED; STARCH, CORN; SODIUM LAURYL SULFATE; TITANIUM DIOXIDE; FD&C YELLOW NO. 6; D&C YELLOW NO. 10 ALUMINUM LAKE; FD&C BLUE NO. 1 ALUMINUM LAKE

WARNING: RISKS FROM CONCOMITANT USE WITH OPIOIDS; ABUSE, MISUSE, AND ADDICTION; DEPENDENCE AND WITHDRAWAL REACTIONS; and SUICIDAL THOUGHTS AND BEHAVIORS

- Concomitant use of benzodiazepines and opioids may result in profound sedation, respiratory depression, coma, and death. Reserve concomitant prescribing of these drugs for patients for whom alternative treatment options are inadequate. Limit dosages and durations to the minimum required. Follow patients for signs and symptoms of respiratory depression and sedation (see WARNINGS and PRECAUTIONS).

- The use of benzodiazepines, including chlordiazepoxide and amitriptyline hydrochloride tablets, exposes users to risks of abuse, misuse, and addiction, which can lead to overdose or death. Abuse and misuse of benzodiazepines commonly involve concomitant use of other medications, alcohol, and/or illicit substances, which is associated with an increased frequency of serious adverse outcomes. Before prescribing chlordiazepoxide and amitriptyline hydrochloride tablets and throughout treatment, assess each patient’s risk for abuse, misuse, and addiction (see WARNINGS).

- The continued use of benzodiazepines, including chlordiazepoxide and amitriptyline hydrochloride tablets, may lead to clinically significant physical dependence. The risks of dependence and withdrawal increase with longer treatment duration and higher daily dose. Abrupt discontinuation or rapid dosage reduction of chlordiazepoxide and amitriptyline hydrochloride tablets after continued use may precipitate acute withdrawal reactions, which can be life-threatening. To reduce the risk of withdrawal reactions, use a gradual taper to discontinue chlordiazepoxide and amitriptyline hydrochloride tablets or reduce the dosage (see DOSAGE AND ADMINISTRATION and WARNINGS).

- Antidepressants increased the risk of suicidal thoughts and behaviors in pediatric and young adult patients in short-term studies. Closely monitor all antidepressant-treated patients for clinical worsening, and for emergence of suicidal thoughts and behaviors (see WARNINGS). Chlordiazepoxide and amitriptyline hydrochloride tablets are not approved for use in pediatric patients (see PRECAUTIONS).

DESCRIPTION

Chlordiazepoxide and amitriptyline hydrochloride tablets, USP combine for oral administration, chlordiazepoxide, an agent for the relief of anxiety and tension, and amitriptyline, an antidepressant.

Chlordiazepoxide, USP is a benzodiazepine with the formula 7-chloro-2-(methylamino)-5-phenyl-3H-1,4-benzodiazepine-4-oxide. It is a yellow crystalline powder and is insoluble in water. The chemical structure is:

Amitriptyline hydrochloride, USP is a dibenzocycloheptadiene derivative. The formula is 10,11-dihydro-N,N-dimethyl-5H-dibenzo[a,d]cycloheptene-Δ^5,γ-propylamine hydrochloride. It is a white or practically white crystalline powder that is freely soluble in water. The chemical structure is:

Each film-coated tablet for oral administration contains 5 mg of chlordiazepoxide and 14 mg of amitriptyline hydrochloride equivalent to 12.5 mg of amitriptyline or 10 mg of chlordiazepoxide and 27.98 mg of amitriptyline hydrochloride equivalent to 25 mg of amitriptyline. Each tablet contains the following inactive ingredients: colloidal silicon dioxide, croscarmellose sodium, hydroxypropyl cellulose, hypromellose, magnesium stearate, microcrystalline cellulose, polyethylene glycol, pregelatinized starch (corn), sodium lauryl sulfate and titanium dioxide. In addition, the 5 mg/12.5 mg tablets also contain D&C Yellow No. 10 Aluminum Lake, FD&C Blue No. 1 Aluminum Lake and FD&C Yellow No. 6 Aluminum Lake and the 10 mg/25 mg tablets also contain polydextrose and triacetin.

CLINICAL PHARMACOLOGY

Both components of chlordiazepoxide and amitriptyline hydrochloride tablets exert their action in the central nervous system. Extensive studies with chlordiazepoxide in many animal species suggest action in the limbic system. Recent evidence indicates that the limbic system is involved in emotional response. Taming action was observed in some species. The mechanism of action of amitriptyline in man is not known, but the drug appears to interfere with the reuptake of norepinephrine into adrenergic nerve endings. This action may prolong the sympathetic activity of biogenic amines.

INDICATIONS AND USAGE

Chlordiazepoxide and amitriptyline hydrochloride tablets are indicated for the treatment of patients with moderate to severe depression associated with moderate to severe anxiety.

The therapeutic response to chlordiazepoxide and amitriptyline hydrochloride tablets occurs earlier and with fewer treatment failures than when either amitriptyline or chlordiazepoxide is used alone.

Symptoms likely to respond in the first week of treatment include: insomnia, feelings of guilt or worthlessness, agitation, psychic and somatic anxiety, suicidal ideation and anorexia.

CONTRAINDICATIONS

Chlordiazepoxide and amitriptyline hydrochloride tablets are contraindicated in patients with hypersensitivity to either benzodiazepines or tricyclic antidepressants. It should not be given concomitantly with a monoamine oxidase inhibitor. Hyperpyretic crises, severe convulsions and deaths have occurred in patients receiving a tricyclic antidepressant and a monoamine oxidase inhibitor simultaneously. When it is desired to replace a monoamine oxidase inhibitor with chlordiazepoxide and amitriptyline hydrochloride tablets, a minimum of 14 days should be allowed to elapse after the former is discontinued. Chlordiazepoxide and amitriptyline hydrochloride tablets should then be initiated cautiously with gradual increase in dosage until optimum response is achieved.

This drug is contraindicated during the acute recovery phase following myocardial infarction.

WARNINGS

Risks from Concomitant Use with Opioids

Concomitant use of benzodiazepines, including chlordiazepoxide and amitriptyline hydrochloride tablets, and opioids may result in profound sedation, respiratory depression, coma, and death. Because of these risks, reserve concomitant prescribing of these drugs in patients for whom alternative treatment options are inadequate.

Observational studies have demonstrated that concomitant use of opioid analgesics and benzodiazepines increases the risk of drug-related mortality compared to use of opioids alone. If a decision is made to prescribe chlordiazepoxide and amitriptyline hydrochloride tablets concomitantly with opioids, prescribe the lowest effective dosages and minimum durations of concomitant use, and follow patients closely for signs and symptoms of respiratory depression and sedation. In patients already receiving an opioid analgesic, prescribe a lower initial dose of chlordiazepoxide and amitriptyline hydrochloride tablets than indicated in the absence of an opioid and titrate based on clinical response. If an opioid is initiated in a patient already taking chlordiazepoxide and amitriptyline hydrochloride tablets, prescribe a lower initial dose of the opioid and titrate based upon clinical response.

Advise both patients and caregivers about the risks of respiratory depression and sedation when chlordiazepoxide and amitriptyline hydrochloride tablets are used with opioids. Advise patients not to drive or operate heavy machinery until the effects of concomitant use with the opioid have been determined (see PRECAUTIONS: Drug-Drug Interactions).

Abuse, Misuse, and Addiction

The use of benzodiazepines, including chlordiazepoxide and amitriptyline hydrochloride tablets, exposes users to the risks of abuse, misuse, and addiction, which can lead to overdose or death. Abuse and misuse of benzodiazepines often (but not always) involve the use of doses greater than the maximum recommended dosage and commonly involve concomitant use of other medications, alcohol, and/or illicit substances, which is associated with an increased frequency of serious adverse outcomes, including respiratory depression, overdose, or death (see DRUG ABUSE AND DEPENDENCE: Abuse).

Before prescribing chlordiazepoxide and amitriptyline hydrochloride tablets and throughout treatment, assess each patient’s risk for abuse, misuse, and addiction (e.g., using a standardized screening tool). Use of chlordiazepoxide and amitriptyline hydrochloride tablets, particularly in patients at elevated risk, necessitates counseling about the risks and proper use of chlordiazepoxide and amitriptyline hydrochloride tablets along with monitoring for signs and symptoms of abuse, misuse, and addiction. Prescribe the lowest effective dosage; avoid or minimize concomitant use of CNS depressants and other substances associated with abuse, misuse, and addiction (e.g., opioid analgesics, stimulants); and advise patients on the proper disposal of unused drug. If a substance use disorder is suspected, evaluate the patient and institute (or refer them for) early treatment, as appropriate.

Dependence and Withdrawal Reactions

To reduce the risk of withdrawal reactions, use a gradual taper to discontinue chlordiazepoxide and amitriptyline hydrochloride tablets or reduce the dosage (a patient-specific plan should be used to taper the dose) (see DOSAGE AND ADMINISTRATION: Discontinuation or Dosage Reduction of Chlordiazepoxide and Amitriptyline Hydrochloride Tablets).

Patients at an increased risk of withdrawal adverse reactions after benzodiazepine discontinuation or rapid dosage reduction include those who take higher dosages, and those who have had longer durations of use.

Acute Withdrawal Reactions

The continued use of benzodiazepines, including chlordiazepoxide and amitriptyline hydrochloride tablets, may lead to clinically significant physical dependence. Abrupt discontinuation or rapid dosage reduction of chlordiazepoxide and amitriptyline hydrochloride tablets after continued use, or administration of flumazenil (a benzodiazepine antagonist) may precipitate acute withdrawal reactions, which can be life-threatening (e.g., seizures) (see DRUG ABUSE AND DEPENDENCE: Dependence).

Protracted Withdrawal Syndrome

In some cases, benzodiazepine users have developed a protracted withdrawal syndrome with withdrawal symptoms lasting weeks to more than 12 months (see DRUG ABUSE AND DEPENDENCE: Dependence).

Suicidal Thoughts and Behaviors in Adolescent and Young Adults

In pooled analyses of placebo-controlled trials of antidepressant drugs (SSRIs and other antidepressant classes) that included approximately 77,000 adult patients and 4,500 pediatric patients, the incidence of suicidal thoughts and behaviors in antidepressant-treated patients age 24 years and younger was greater than in placebo-treated patients. There was considerable variation in risk of suicidal thoughts and behaviors among drugs, but there was an increased risk identified in young patients for most drugs studied. There were differences in absolute risk of suicidal thoughts and behaviors across the different indications, with the highest incidence in patients with MDD. The drug-placebo differences in the number of cases of suicidal thoughts and behaviors per 1,000 patients treated are provided in Table 1.

Table 1: Risk Differences of the Number of Patients of Suicidal Thoughts and Behavior in the Pooled Placebo-Controlled Trials of Antidepressants in Pediatric and Adult Patients
Age Range | Drug-Placebo Difference in Number of Patients of Suicidal Thoughts or Behaviors per 1,000 Patients Treated
 | Increases Compared to Placebo
< 18 years old | 14 additional patients
18 to 24 years old | 5 additional patients
 | Decreases Compared to Placebo
25 to 64 years old | 1 fewer patient
≥ 65 years old | 6 fewer patients

It is unknown whether the risk of suicidal thoughts and behaviors in children, adolescents, and young adults extends to longer-term use, i.e., beyond four months. However, there is substantial evidence from placebo-controlled maintenance trials in adults with MDD that antidepressants delay the recurrence of depression and that depression itself is a risk factor for suicidal thoughts and behaviors.

Monitor all antidepressant-treated patients for any indication for clinical worsening and emergence of suicidal thoughts and behaviors, especially during the initial few months of drug therapy, and at times of dosage changes. Counsel family members or caregivers of patients to monitor for changes in behavior and to alert the healthcare provider. Consider changing the therapeutic regimen, including possibly discontinuing chlordiazepoxide and amitriptyline hydrochloride tablets, in patients whose depression is persistently worse, or who are experiencing emergent suicidal thoughts or behaviors.

Serotonin Syndrome

The development of a potentially life-threatening serotonin syndrome has been reported with tricyclic antidepressants, including chlordiazepoxide and amitriptyline hydrochloride tablets, alone but particularly with concomitant use of other serotonergic drugs (including triptans, tricyclic antidepressants, SSRI/SNRI, fentanyl, lithium, tramadol, tryptophan, buspirone, and St. John’s Wort) and with drugs that impair metabolism of serotonin (in particular, MAOIs, both those intended to treat psychiatric disorders and also others, such as linezolid and intravenous methylene blue). Serotonin syndrome symptoms may include mental status changes (e.g., agitation, hallucinations, delirium, and coma), autonomic instability (e.g., tachycardia, labile blood pressure, dizziness, diaphoresis, flushing, hyperthermia), neuromuscular changes (e.g., tremor, rigidity, myoclonus, hyperreflexia, incoordination), seizures, and/or gastrointestinal symptoms (e.g., nausea, vomiting, diarrhea). Patients should be monitored for the emergence of serotonin syndrome.

The concomitant use of chlordiazepoxide and amitriptyline hydrochloride tablets with MAOIs intended to treat psychiatric disorders is contraindicated. Chlordiazepoxide and amitriptyline hydrochloride tablets should also not be started in a patient who is being treated with MAOIs such as linezolid or intravenous methylene blue. All reports with methylene blue that provided information on the route of administration involved intravenous administration in the dose range of 1 mg/kg to 8 mg/kg. No reports involved the administration of methylene blue by other routes (such as oral tablets or local tissue injection) or at lower doses. There may be circumstances when it is necessary to initiate treatment with an MAOI such as linezolid or intravenous methylene blue in a patient taking chlordiazepoxide and amitriptyline hydrochloride tablets. Chlordiazepoxide and amitriptyline hydrochloride tablets should be discontinued before initiating treatment with the MAOI (see CONTRAINDICATIONS and DOSAGE AND ADMINISTRATION). If concomitant use of chlordiazepoxide and amitriptyline hydrochloride tablets with other serotonergic drugs, including triptans, tricyclic antidepressants, fentanyl, lithium, tramadol, buspirone, tryptophan, and St. John’s Wort is clinically warranted, patients should be made aware of a potential increased risk for serotonin syndrome, particularly during treatment initiation and dose increases. Treatment with chlordiazepoxide and amitriptyline hydrochloride tablets and any concomitant serotonergic agents should be discontinued immediately if the above events occur and supportive symptomatic treatment should be initiated.

Activation of Mania or Hypomania

In patients with bipolar disorder, treating a depressive episode with chlordiazepoxide and amitriptyline hydrochloride tablets or another antidepressant may precipitate a mixed/manic episode. Prior to initiating treatment with chlordiazepoxide and amitriptyline hydrochloride tablets, screen patients for any personal or family history of bipolar disorder, mania, or hypomania.

Hyponatremia

Hyponatremia has occurred as a result of treatment with chlordiazepoxide and amitriptyline hydrochloride tablets. In many cases, hyponatremia appears to be the result of the syndrome of inappropriate antidiuretic hormone secretion (SIADH). Signs and symptoms of hyponatremia include headache, difficulty concentrating, memory impairment, confusion, weakness, and unsteadiness, which may lead to falls. Signs and symptoms associated with more severe and/or acute cases have included syncope, seizure, coma, respiratory arrest, and death.

In patients with symptomatic hyponatremia, discontinue chlordiazepoxide and amitriptyline hydrochloride tablets and institute appropriate medical intervention. Elderly patients, patients taking diuretics, and those who are volume-depleted may be at greater risk of developing hyponatremia with chlordiazepoxide and amitriptyline hydrochloride tablets.

Angle-Closure Glaucoma

The pupillary dilation that occurs following use of many antidepressant drugs including chlordiazepoxide and amitriptyline hydrochloride tablets may trigger an angle closure attack in a patient with anatomically narrow angles who does not have a patent iridectomy.

General

Because of the atropine-like action of the amitriptyline component, great care should be used in treating patients with a history of urinary retention or angle-closure glaucoma. In patients with glaucoma, even average doses may precipitate an attack. Severe constipation may occur in patients taking tricyclic antidepressants in combination with anticholinergic-type drugs.

Patients with cardiovascular disorders should be watched closely. Tricyclic antidepressant drugs, particularly when given in high doses, have been reported to produce arrhythmias, sinus tachycardia and prolongation of conduction time. Myocardial infarction and stroke have been reported in patients receiving drugs of this class.

Because of the sedative effects of chlordiazepoxide and amitriptyline hydrochloride tablets, patients should be cautioned about combined effects with alcohol or other CNS depressants. The additive effects may produce a harmful level of sedation and CNS depression.

Patients receiving chlordiazepoxide and amitriptyline hydrochloride tablets should be cautioned against engaging in hazardous occupations requiring complete mental alertness, such as operating machinery or driving a motor vehicle.

Neonatal Sedation and Withdrawal Syndrome

Use of chlordiazepoxide and amitriptyline hydrochloride tablets late in pregnancy can result in sedation (respiratory depression, lethargy, hypotonia) and/or withdrawal symptoms (hyperreflexia, irritability, restlessness, tremors, inconsolable crying, and feeding difficulties) in the neonate (see PRECAUTIONS: Pregnancy). Monitor neonates exposed to chlordiazepoxide and amitriptyline hydrochloride tablets during pregnancy or labor for signs of sedation and monitor neonates exposed to chlordiazepoxide and amitriptyline hydrochloride tablets during pregnancy for signs of withdrawal; manage these neonates accordingly.

PRECAUTIONS

General

Use with caution in patients with a history of seizures.

Close supervision is required when chlordiazepoxide and amitriptyline hydrochloride tablets are given to hyperthyroid patients or those on thyroid medication.

The usual precautions should be observed when treating patients with impaired renal or hepatic function.

Patients with suicidal ideation should not have easy access to large quantities of the drug. The possibility of suicide in depressed patients remains until significant remission occurs.

Information for Patients

Advise the patient to read the FDA-approved patient labeling (Medication Guide).

Risks from Concomitant Use with Opioids

Advise both patients and caregivers about the risks of potentially fatal respiratory depression and sedation when chlordiazepoxide and amitriptyline hydrochloride tablets are used with opioids and not to use such drugs concomitantly unless supervised by a health care provider. Advise patients not to drive or operate heavy machinery until the effects of concomitant use with the opioid have been determined (see WARNINGS: Risks from Concomitant Use with Opioids and PRECAUTIONS: Drug Interactions).

Abuse, Misuse, and Addiction

Inform patients that the use of chlordiazepoxide and amitriptyline hydrochloride tablets, even at recommended dosages, exposes users to risks of abuse, misuse, and addiction, which can lead to overdose and death, especially when used in combination with other medications (e.g., opioid analgesics), alcohol, and/or illicit substances. Inform patients about the signs and symptoms of benzodiazepine abuse, misuse, and addiction; to seek medical help if they develop these signs and/or symptoms; and on the proper disposal of unused drug (see WARNINGS: Abuse, Misuse, and Addiction and DRUG ABUSE AND DEPENDENCE).

Withdrawal Reactions

Inform patients that the continued use of chlordiazepoxide and amitriptyline hydrochloride tablets may lead to clinically significant physical dependence and that abrupt discontinuation or rapid dosage reduction of chlordiazepoxide and amitriptyline hydrochloride tablets may precipitate acute withdrawal reactions, which can be life-threatening. Inform patients that in some cases, patients taking benzodiazepines have developed a protracted withdrawal syndrome with withdrawal symptoms lasting weeks to more than 12 months. Instruct patients that discontinuation or dosage reduction of chlordiazepoxide and amitriptyline hydrochloride tablets may require a slow taper (see WARNINGS: Dependence and Withdrawal Reactions and DRUG ABUSE AND DEPENDENCE).

Suicidal Thoughts and Behaviors

Advise patients and caregivers to look for the emergence of suicidal thoughts and behaviors, especially early during treatment and when the dosage is adjusted up or down (see WARNINGS: Suicidal Thoughts and Behaviors in Adolescents and Young Adults).

Pregnancy

Advise pregnant females that use of chlordiazepoxide and amitriptyline hydrochloride tablets late in pregnancy can result in sedation (respiratory depression, lethargy, hypotonia) and/or withdrawal symptoms (hyperreflexia, irritability, restlessness, tremors, inconsolable crying, and feeding difficulties) in newborns (see WARNINGS: Neonatal Sedation and Withdrawal Syndrome and Precautions, Pregnancy). Instruct patients to inform their healthcare provider if they are pregnant.

Advise patients that there is a pregnancy exposure registry that monitors pregnancy outcomes in women exposed to chlordiazepoxide and amitriptyline hydrochloride tablets during pregnancy (see PRECAUTIONS: Pregnancy).

Nursing

Advise patients that breastfeeding is not recommended during treatment with chlordiazepoxide and amitriptyline hydrochloride tablets (see PRECAUTIONS: Nursing Mothers).

Essential Laboratory Tests

Patients on prolonged treatment should have periodic liver function tests and blood counts.

Drug-Drug Interactions

The concomitant use of benzodiazepines and opioids increases the risk of respiratory depression because of actions at different receptor sites in the CNS that control respiration. Benzodiazepines interact at GABAA sites and opioids interact primarily at mu receptors. When benzodiazepines and opioids are combined, the potential for benzodiazepines to significantly worsen opioid-related respiratory depression exists. Limit dosage and duration of concomitant use of benzodiazepines and opioids, and monitor patients closely for respiratory depression and sedation.

Topiramate

Some patients may experience a large increase in amitriptyline concentration in the presence of topiramate and any adjustments in amitriptyline dose should be made according to the patient's clinical response and not on the basis of plasma levels.

Drug and Treatment Interactions

Because of its amitriptyline component, chlordiazepoxide and amitriptyline hydrochloride tablets may block the antihypertensive action of guanethidine or compounds with a similar mechanism of action.

Drugs Metabolized by P450 2D6

The biochemical activity of the drug metabolizing isozyme cytochrome P450 2D6 (debrisoquin hydroxylase) is reduced in a subset of the Caucasian population (about 7% to 10% of Caucasians are so called “poor metabolizers”); reliable estimates of the prevalence of reduced P450 2D6 isozyme activity among Asian, African and other populations are not yet available. Poor metabolizers have higher than expected plasma concentrations of tricyclic antidepressants (TCAs) when given usual doses. Depending on the fraction of drug metabolized by P450 2D6, the increase in plasma concentration may be small or quite large (8-fold increase in plasma AUC of the TCA).

In addition, certain drugs inhibit the activity of this isozyme and make normal metabolizers resemble poor metabolizers. An individual who is stable on a given dose of TCA may become abruptly toxic when given one of these inhibiting drugs as concomitant therapy. The drugs that inhibit cytochrome P450 2D6 include some that are not metabolized by the enzyme (quinidine; cimetidine) and many that are substrates for P450 2D6 (many other antidepressants, phenothiazines, and the type 1c antiarrhythmics propafenone and flecainide). While all the selective serotonin reuptake inhibitors (SSRIs), e.g., fluoxetine, sertraline and paroxetine, inhibit P450 2D6, they may vary in the extent of inhibition. The extent to which SSRI TCA interactions may pose clinical problems will depend on the degree of inhibition and the pharmacokinetics of the SSRI involved. Nevertheless, caution is indicated in the coadministration of TCAs with any of the SSRIs and also in switching from one class to the other. Of particular importance, sufficient time must elapse before initiating TCA treatment in a patient being withdrawn from fluoxetine, given the long half-life of the parent and active metabolite (at least 5 weeks may be necessary).

Concomitant use of tricyclic antidepressants with drugs that can inhibit cytochrome P450 2D6 may require lower doses than usually prescribed for either the tricyclic antidepressant or the other drug. Furthermore, whenever one of these other drugs is withdrawn from cotherapy, an increased dose of tricyclic antidepressant may be required. It is desirable to monitor TCA plasma levels whenever a TCA is going to be coadministered with another drug known to be an inhibitor of P450 2D6.

The effects of concomitant administration of chlordiazepoxide and amitriptyline hydrochloride tablets and other psychotropic drugs have not been evaluated. Sedative effects may be additive.

Cimetidine is reported to reduce hepatic metabolism of certain tricyclic antidepressants and benzodiazepines, thereby delaying elimination and increasing steady-state concentrations of these drugs. Clinically significant effects have been reported with the tricyclic antidepressants when used concomitantly with cimetidine (Tagamet®).

The drug should be discontinued several days before elective surgery.

Concurrent administration of ECT and chlordiazepoxide and amitriptyline hydrochloride tablets should be limited to those patients for whom it is essential.

Pregnancy

Pregnancy Exposure Registry

There is a pregnancy registry that monitors pregnancy outcomes in women exposed to psychiatric medications, including chlordiazepoxide and amitriptyline hydrochloride tablets, during pregnancy. Healthcare providers are encouraged to register patients by calling the National Pregnancy Registry for Psychiatric Medications at 1-866-961-2388 or visiting online at https://womensmentalhealth.org/pregnancyregistry/.

Risk Summary

Neonates born to mothers using benzodiazepines late in pregnancy have been reported to experience symptoms of sedation and/or neonatal withdrawal (see WARNINGS: Neonatal Sedation and Withdrawal Syndrome, and Clinical Considerations). Available data from published observational studies of pregnant women exposed to benzodiazepines do not report a clear association with benzodiazepines and major birth defects (see Data).

The background risk of major birth defects and miscarriage for the indicated population is unknown. All pregnancies have a background risk of birth defect, loss, or other adverse outcomes. In the U.S. general population, the estimated risk of major birth defects and of miscarriage in clinically recognized pregnancies is 2% to 4% and 15% to 20%, respectively.

Clinical Considerations

Fetal/Neonatal Adverse Reactions

Benzodiazepines cross the placenta and may produce respiratory depression, hypotonia and sedation in neonates. Monitor neonates exposed to chlordiazepoxide and amitriptyline hydrochloride tablets during pregnancy or labor for signs of sedation, respiratory depression, hypotonia, and feeding problems. Monitor neonates exposed to chlordiazepoxide and amitriptyline hydrochloride tablets during pregnancy for signs of withdrawal. Manage these neonates accordingly (see WARNINGS: Neonatal Sedation and Withdrawal Syndrome).

Data

Human Data

Published data from observational studies on the use of benzodiazepines during pregnancy do not report a clear association with benzodiazepines and major birth defects. Although early studies reported an increased risk of congenital malformations with diazepam and chlordiazepoxide, there was no consistent pattern noted. In addition, the majority of more recent case-control and cohort studies of benzodiazepine use during pregnancy, which were adjusted for confounding exposures to alcohol, tobacco and other medications, have not confirmed these findings.

Nursing Mothers

Risk Summary

It is not known whether this drug is excreted in human milk. There are reports of sedation, poor feeding and poor weight gain in infants exposed to benzodiazepines through breast milk. Because of the potential for serious adverse reaction, including sedation and withdrawal symptoms in breastfed infants, advise patients that breastfeeding is not recommended during treatment with chlordiazepoxide and amitriptyline hydrochloride tablets.

Pediatric Use

Safety and effectiveness in the pediatric population have not been established (see BOX WARNING and WARNINGS: Suicidal Thoughts and Behaviors in Adolescents and Young Adults).

Anyone considering the use of chlordiazepoxide and amitriptyline hydrochloride tablets in a child or adolescent must balance the potential risks with the clinical need.

Geriatric Use

In elderly and debilitated patients it is recommended that dosage be limited to the smallest effective amount to preclude the development of ataxia, oversedation, confusion or anticholinergic effects.

Of the total number of subjects in clinical studies of chlordiazepoxide and amitriptyline hydrochloride tablets, 74 individuals were 65 years and older. An additional 34 subjects were between 60 and 69 years of age. No overall differences in safety and effectiveness were observed between these subjects and younger subjects, and other reported clinical experience has not identified differences in responses between the elderly and younger patients, but greater sensitivity of some older individuals cannot be ruled out.

The active ingredients in chlordiazepoxide and amitriptyline hydrochloride tablets are known to be substantially excreted by the kidney and the risk of toxic reactions to this drug may be greater in patients with impaired renal function. Because elderly patients are more likely to have decreased renal function, care should be taken in dose selection and it may be useful to monitor renal function.

Sedating drugs may cause confusion and over-sedation in the elderly; elderly patients generally should be started on low doses of chlordiazepoxide and amitriptyline hydrochloride tablets and observed closely.

Clinical studies of chlordiazepoxide and amitriptyline hydrochloride tablets did not include sufficient numbers of subjects aged 65 years and older to determine whether they respond differently than younger subjects. Other reported clinical experience has not identified differences in responses between the elderly and younger patients. In general, dose selection for an elderly patient should be cautious, usually starting at the low end of the dosing range, reflecting the greater frequency of decreased hepatic, renal or cardiac function and of concomitant disease or other drug therapy.

ADVERSE REACTIONS

Adverse reactions to chlordiazepoxide and amitriptyline hydrochloride are those associated with the use of either component alone. Most frequently reported were drowsiness, dry mouth, constipation, blurred vision, dizziness and bloating. Other side effects occurring less commonly included vivid dreams, impotence, tremor, confusion and nasal congestion. Many symptoms common to the depressive state, such as anorexia, fatigue, weakness, restlessness and lethargy, have been reported as side effects of treatment with both chlordiazepoxide and amitriptyline hydrochloride tablets and amitriptyline.

Granulocytopenia, jaundice and hepatic dysfunction of uncertain etiology have also been observed rarely with chlordiazepoxide and amitriptyline hydrochloride tablets. When treatment with chlordiazepoxide and amitriptyline hydrochloride tablets is prolonged, periodic blood counts and liver function tests are advisable.

Note

Included in the listing which follows are adverse reactions which have not been reported with chlordiazepoxide and amitriptyline hydrochloride. However, they are included because they have been reported during therapy with one or both of the components or closely related drugs.

Cardiovascular: Hypotension, hypertension, tachycardia, palpitations, myocardial infarction, arrhythmias, heart block, stroke.

Psychiatric: Euphoria, apprehension, poor concentration, delusions, hallucinations, hypomania and increased or decreased libido.

Neurologic: Incoordination, ataxia, numbness, tingling and paresthesias of the extremities, extrapyramidal symptoms, syncope, changes in EEG patterns.

Anticholinergic: Disturbance of accommodation, paralytic ileus, urinary retention, dilatation of urinary tract.

Allergic: Skin rash, urticaria, photosensitization, edema of face and tongue, pruritus, drug reaction with eosinophilia and systemic symptoms (DRESS).

Hematologic: Bone marrow depression including agranulocytosis, eosinophilia, purpura, thrombocytopenia.

Gastrointestinal: Nausea, epigastric distress, vomiting, anorexia, stomatitis, peculiar taste, diarrhea, black tongue.

Endocrine: Testicular swelling and gynecomastia in the male, breast enlargement, galactorrhea and minor menstrual irregularities in the female, elevation and lowering of blood sugar levels, and syndrome of inappropriate ADH (antidiuretic hormone) secretion.

Other: Headache, weight gain or loss, increased perspiration, urinary frequency, mydriasis, jaundice, alopecia, parotid swelling, hyponatremia.

DRUG ABUSE AND DEPENDENCE

Controlled Substance

Chlordiazepoxide and amitriptyline hydrochloride tablets contain chlordiazepoxide, a Schedule IV controlled substance.

Abuse

Chlordiazepoxide and amitriptyline hydrochloride tablets are a benzodiazepine and a CNS depressant with a potential for abuse and addiction. Abuse is the intentional, non-therapeutic use of a drug, even once, for its desirable psychological or physiological effects. Misuse is the intentional use, for therapeutic purposes, of a drug by an individual in a way other than prescribed by a health care provider or for whom it was not prescribed. Drug addiction is a cluster of behavioral, cognitive, and physiological phenomena that may include a strong desire to take the drug, difficulties in controlling drug use (e.g., continuing drug use despite harmful consequences, giving a higher priority to drug use than other activities and obligations), and possible tolerance or physical dependence. Even taking benzodiazepines as prescribed may put patients at risk for abuse and misuse of their medication. Abuse and misuse of benzodiazepines may lead to addiction.

Abuse and misuse of benzodiazepines often (but not always) involve the use of doses greater than the maximum recommended dosage and commonly involve concomitant use of other medications, alcohol, and/or illicit substances, which is associated with an increased frequency of serious adverse outcomes, including respiratory depression, overdose, or death. Benzodiazepines are often sought by individuals who abuse drugs and other substances, and by individuals with addictive disorders (see WARNINGS: Abuse, Misuse, and Addiction).

The following adverse reactions have occurred with benzodiazepine abuse and/or misuse: abdominal pain, amnesia, anorexia, anxiety, aggression, ataxia, blurred vision, confusion, depression, disinhibition, disorientation, dizziness, euphoria, impaired concentration and memory, indigestion, irritability, muscle pain, slurred speech, tremors, and vertigo.

The following severe adverse reactions have occurred with benzodiazepine abuse and/or misuse: delirium, paranoia, suicidal ideation and behavior, seizures, coma, breathing difficulty, and death. Death is more often associated with polysubstance use (especially benzodiazepines with other CNS depressants such as opioids and alcohol).

Dependence

Physical Dependence

Chlordiazepoxide and amitriptyline hydrochloride tablets may produce physical dependence from continued therapy. Physical dependence is a state that develops as a result of physiological adaptation in response to repeated drug use, manifested by withdrawal signs and symptoms after abrupt discontinuation or a significant dose reduction of a drug. Abrupt discontinuation or rapid dosage reduction of benzodiazepines or administration of flumazenil, a benzodiazepine antagonist, may precipitate acute withdrawal reactions, including seizures, which can be life-threatening. Patients at an increased risk of withdrawal adverse reactions after benzodiazepine discontinuation or rapid dosage reduction include those who take higher dosages (i.e., higher and/or more frequent doses) and those who have had longer durations of use (see WARNINGS: Dependence and Withdrawal Reactions).

To reduce the risk of withdrawal reactions, use a gradual taper to discontinue chlordiazepoxide and amitriptyline hydrochloride tablets or reduce the dosage (see DOSAGE AND ADMINISTRATION: Discontinuation or Dosage Reduction of Chlordiazepoxide and Amitriptyline Hydrochloride Tablets and WARNINGS: Dependence and Withdrawal Reactions).

Acute withdrawal signs and symptoms associated with benzodiazepines have included abnormal involuntary movements, anxiety, blurred vision, depersonalization, depression, derealization, dizziness, fatigue, gastrointestinal adverse reactions (e.g., nausea, vomiting, diarrhea, weight loss, decreased appetite), headache, hyperacusis, hypertension, irritability, insomnia, memory impairment, muscle pain and stiffness, panic attacks, photophobia, restlessness, tachycardia, and tremor. More severe acute withdrawal signs and symptoms, including life-threatening reactions, have included catatonia, convulsions, delirium tremens, depression, hallucinations, mania, psychosis, seizures, and suicidality.

Protracted withdrawal syndrome associated with benzodiazepines is characterized by anxiety, cognitive impairment, depression, insomnia, formication, motor symptoms (e.g., weakness, tremor, muscle twitches), paresthesia, and tinnitus that persists beyond 4 to 6 weeks after initial benzodiazepine withdrawal. Protracted withdrawal symptoms may last weeks to more than 12 months. As a result, there may be difficulty in differentiating withdrawal symptoms from potential re-emergence or continuation of symptoms for which the benzodiazepine was being used.

Tolerance

Tolerance to chlordiazepoxide and amitriptyline hydrochloride tablets may develop from continued therapy. Tolerance is a physiological state characterized by a reduced response to a drug after repeated administration (i.e., a higher dose of a drug is required to produce the same effect that was once obtained at a lower dose). Tolerance to the therapeutic effect of chlordiazepoxide and amitriptyline hydrochloride tablets may develop; however, little tolerance develops to the amnestic reactions and other cognitive impairments caused by benzodiazepines.

OVERDOSAGE

Overdosage of chlordiazepoxide and amitriptyline hydrochloride tablets, which contain a benzodiazepine (chlordiazepoxide) and a tricyclic antidepressant (amitriptyline hydrochloride), may manifest signs and symptoms related to either of its components. Deaths may occur from overdosage with this class of drugs. Multiple drug ingestion (including alcohol) is common in deliberate tricyclic antidepressant overdose. Signs and symptoms of toxicity develop rapidly after tricyclic antidepressant overdose.

Critical manifestations of tricyclic antidepressant overdosage include cardiac dysrhythmias, severe hypotension, convulsions and CNS depression, including coma. Changes in the electrocardiogram, particularly in QRS axis or width, are clinically significant indicators of tricyclic antidepressant toxicity. Obtain an ECG and immediately initiate cardiac monitoring; hospital monitoring is required as soon as possible.

Other signs of overdosage may include confusion, disturbed concentration, transient visual hallucinations, dilated pupils, agitation, hyperactive reflexes, stupor, drowsiness, muscle rigidity, vomiting, hypothermia, hyperpyrexia or any of the symptoms listed under ADVERSE REACTIONS.

Overdosage of benzodiazepines is characterized by central nervous system depression ranging from drowsiness to coma. In mild to moderate cases, symptoms can include drowsiness, confusion, dysarthria, lethargy, hypnotic state, diminished reflexes, ataxia, and hypotonia. Rarely, paradoxical or disinhibitory reactions (including agitation, irritability, impulsivity, violent behavior, confusion, restlessness, excitement, and talkativeness) may occur. In severe overdosage cases, patients may develop respiratory depression and coma. Overdosage of benzodiazepines in combination with other CNS depressants (including alcohol and opioids) may be fatal (see WARNINGS: Abuse, Misuse, and Addiction). Markedly abnormal (lowered or elevated) blood pressure, heart rate, or respiratory rate raise the concern that additional drugs and/or alcohol are involved in the overdosage.

In managing benzodiazepine overdosage, employ general supportive measures, including intravenous fluids and airway management. Flumazenil, a specific benzodiazepine receptor antagonist indicated for the complete or partial reversal of the sedative effects of benzodiazepines in the management of benzodiazepine overdosage, can lead to withdrawal and adverse reactions, including seizures with chlordiazepoxide and amitriptyline hydrochloride tablets because overdosage with amitriptyline and other tricyclic and tetracyclic antidepressants increases the risk of seizures. Seizure risk is also increased in patients with long-term benzodiazepine use and physical dependency. The risk of withdrawal seizures with flumazenil use also may be increased in patients with epilepsy. Flumazenil is contraindicated in patients who have received a benzodiazepine for control of a potentially life-threatening condition (e.g., status epilepticus).

Contact the Poison Help line (1-800-222-1222) or medical toxicologist for additional overdosage management recommendations.

DOSAGE AND ADMINISTRATION

Optimum dosage varies with the severity of the symptoms and the response of the individual patient. When a satisfactory response is obtained, dosage should be reduced to the smallest amount needed to maintain the remission. The larger portion of the total daily dose may be taken at bedtime. In some patients, a single dose at bedtime may be sufficient. In general, lower dosages are recommended for elderly patients.

Chlordiazepoxide and amitriptyline hydrochloride tablets 10 mg/25 mg are recommended in an initial dosage of 3 or 4 tablets daily in divided doses; this may be increased to 6 tablets daily as required. Some patients respond to smaller doses and can be maintained on 2 tablets daily.

Chlordiazepoxide and amitriptyline hydrochloride tablets 5 mg/12.5 mg in an initial dosage of 3 or 4 tablets daily in divided doses may be satisfactory in patients who do not tolerate higher doses.

Screen for Bipolar Disorder Prior to Starting Chlordiazepoxide and Amitriptyline Hydrochloride Tablets

Prior to initiating treatment with chlordiazepoxide and amitriptyline hydrochloride tablets or another antidepressant, screen patients for a personal or family history of bipolar disorder, mania, or hypomania (see WARNINGS: Activation of Mania or Hypomania).

Discontinuation or Dosage Reduction of Chlordiazepoxide and Amitriptyline Hydrochloride Tablets

To reduce the risk of withdrawal reactions, use a gradual taper to discontinue chlordiazepoxide and amitriptyline hydrochloride tablets or reduce the dosage. If a patient develops withdrawal reactions, consider pausing the taper or increasing the dosage to the previous tapered dosage level. Subsequently decrease the dosage more slowly (see WARNINGS: Dependence and Withdrawal Reactions and DRUG ABUSE AND DEPENDENCE: Dependence).

HOW SUPPLIED

Chlordiazepoxide and Amitriptyline Hydrochloride Tablets, USP are available containing 5 mg of chlordiazepoxide, USP and 14 mg of amitriptyline hydrochloride, USP equivalent to 12.5 mg of amitriptyline or 10 mg of chlordiazepoxide, USP and 27.98 mg of amitriptyline hydrochloride, USP equivalent to 25 mg of amitriptyline.

The 5 mg/12.5 mg tablets are green, film-coated, round, unscored tablets debossed with MYLAN on one side of the tablet and 211 on the other side. They are available as follows:

NDC 0378-0211-01
bottles of 100 tablets

NDC 0378-0211-05
bottles of 500 tablets

The 10 mg/25 mg tablets are white, film-coated, round, unscored tablets debossed with MYLAN on one side of the tablet and 277 on the other side. They are available as follows:

NDC 0378-0277-01
bottles of 100 tablets

NDC 0378-0277-05
bottles of 500 tablets

Store at 20° to 25°C (68° to 77°F). [See USP Controlled Room Temperature.]

Store in a dry place.

Dispense in a tight, light-resistant container as defined in the USP using a child-resistant closure.

PHARMACIST: Dispense a Medication Guide with each prescription.

Medication Guide

Chlordiazepoxide and Amitriptyline Hydrochloride Tablets, USP CIV
(klorʺ dye azʺ e poxʹ ide amʺ i tripʹ ti leen hyeʺ droe klorʹ ide)

What is the most important information I should know about chlordiazepoxide and amitriptyline hydrochloride tablets?

- Chlordiazepoxide is a benzodiazepine medicine. Taking benzodiazepines with opioid medicines, alcohol, or other central nervous system (CNS) depressants (including street drugs) can cause severe drowsiness, breathing problems (respiratory depression), coma and death. Get emergency help right away if any of the following happens:
  - shallow or slowed breathing
  - breathing stops (which may lead to the heart stopping)
  - excessive sleepiness (sedation)
Do not drive or operate heavy machinery until you know how taking chlordiazepoxide and amitriptyline hydrochloride tablets with opioids affect you.
- Risk of abuse, misuse, and addiction. There is a risk of abuse, misuse, and addiction with benzodiazepines, including chlordiazepoxide and amitriptyline hydrochloride tablets, which can lead to overdose and serious side effects including coma and death.
  - Serious side effects including coma and death have happened in people who have abused or misused benzodiazepines, including chlordiazepoxide and amitriptyline hydrochloride tablets. These serious side effects may also include delirium, paranoia, suicidal thoughts or actions, seizures, and difficulty breathing. Call your healthcare provider or go to the nearest hospital emergency room right away if you get any of these serious side effects.
  - You can develop an addiction even if you take chlordiazepoxide and amitriptyline hydrochloride tablets exactly as prescribed by your healthcare provider.
  - Take chlordiazepoxide and amitriptyline hydrochloride tablets exactly as your healthcare provider prescribed.
  - Do not share your chlordiazepoxide and amitriptyline hydrochloride tablets with other people.
  - Keep chlordiazepoxide and amitriptyline hydrochloride tablets in a safe place and away from children.
- Physical dependence and withdrawal reactions. Chlordiazepoxide and amitriptyline hydrochloride tablets can cause physical dependence and withdrawal reactions.
  - Do not suddenly stop taking chlordiazepoxide and amitriptyline hydrochloride tablets. Stopping chlordiazepoxide and amitriptyline hydrochloride tablets suddenly can cause serious and life-threatening side effects, including, unusual movements, responses, or expressions, seizures, sudden and severe mental or nervous system changes, depression, seeing or hearing things that others do not see or hear, an extreme increase in activity or talking, losing touch with reality, and suicidal thoughts or actions. Call your healthcare provider or go to the nearest hospital emergency room right away if you get any of these symptoms.
  - Some people who suddenly stop benzodiazepines have symptoms that can last for several weeks to more than 12 months, including, anxiety, trouble remembering, learning, or concentrating, depression, problems sleeping, feeling like insects are crawling under your skin, weakness, shaking, muscle twitching, burning or prickling feeling in your hands, arms, legs or feet, and ringing in your ears.
  - Physical dependence is not the same as drug addiction. Your healthcare provider can tell you more about the differences between physical dependence and drug addiction.
  - Do not take more chlordiazepoxide and amitriptyline hydrochloride tablets than prescribed or take chlordiazepoxide and amitriptyline hydrochloride tablets for longer than prescribed.
- Increased risk of suicidal thoughts or actions in children, adolescents and young adults. Chlordiazepoxide and amitriptyline hydrochloride tablets and other antidepressant medicines may increase suicidal thoughts or actions in some people 24 years of age and younger, especially within the first few months of treatment or when the dose is changed.
  - Depression or other serious mental illnesses are the most important cause of suicidal thoughts or actions. Some people may have a higher risk of having suicidal thoughts or actions. These include people who have (or have a family history of) depression, bipolar illness (also called manic-depressive illness), or a history of suicidal thoughts or actions.
How can I watch for and try to prevent suicidal thoughts and actions in myself or a family member?
  1. Pay close attention to any changes, especially sudden changes in mood, behavior, thoughts, or feelings or if you or your family member develop suicidal thoughts or actions. This is very important when an antidepressant medicine is started or when the dose is changed.
  2. Call your healthcare provider right away to report new or sudden changes in mood, behavior, thoughts, or feelings or if you or your family member develop suicidal thoughts or actions.
  3. Keep all follow-up visits with your healthcare provider and call between visits if you are worried about symptoms.
Call your healthcare provider right away if you or your family member have any of the following symptoms, especially if they are new, worse, or worry you:

- thoughts about suicide or dying
- new or worse depression
- feeling agitated or restless
- trouble sleeping
- acting aggressive, being angry or violent
- other unusual changes in behavior or mood

- attempts to commit suicide
- new or worse anxiety or irritability
- an extreme increase in activity and talking
- new or worse panic attacks
- acting on dangerous impulses

- Serotonin Syndrome. This condition can be life-threatening and symptoms may include:
  - agitation, hallucinations, coma, or other changes in mental status
  - racing heartbeat, high or low blood pressure
  - coordination problems or muscle twitching (overactive reflexes)
  - nausea, vomiting, or diarrhea
  - sweating or fever
  - muscle rigidity

What are chlordiazepoxide and amitriptyline hydrochloride tablets?

- Chlordiazepoxide and amitriptyline hydrochloride tablets are a prescription medicine used to treat moderate to severe depression that can happen with moderate to severe anxiety.
- Chlordiazepoxide and amitriptyline hydrochloride tablets are a federal controlled substance (C-IV) because they contain chlordiazepoxide that can be abused or lead to dependence. Keep chlordiazepoxide and amitriptyline hydrochloride tablets in a safe place to prevent misuse and abuse. Selling or giving away chlordiazepoxide and amitriptyline hydrochloride tablets may harm others, and is against the law. Tell your healthcare provider if you have ever abused or been dependent on alcohol, prescription medicines or street drugs.
- It is not known if chlordiazepoxide and amitriptyline hydrochloride tablets are safe and effective in children.

Do not take chlordiazepoxide and amitriptyline hydrochloride tablets if you:

- are allergic to chlordiazepoxide and amitriptyline hydrochloride or any of the ingredients in chlordiazepoxide and amitriptyline hydrochloride tablets. See the end of this Medication Guide for a complete list of ingredients in chlordiazepoxide and amitriptyline hydrochloride tablets.
- have had an allergic reaction to other benzodiazepines or tricyclic antidepressant medicines
- take a medicine called a Monoamine Oxidase Inhibitor (MAOI). Ask your healthcare provider or pharmacist if you are not sure if you take an MAOI.
- are recovering from a heart attack

Before you take chlordiazepoxide and amitriptyline hydrochloride tablets, tell your healthcare provider about all of your medical conditions, including if you:

- have or have a family history of suicide, bipolar disorder, or depression
- have a history of drug or alcohol abuse or addiction
- have eye problems
- have problems urinating or emptying your bladder
- have kidney or liver problems
- have or had heart problems, including heart attack or a stroke
- have or have had seizures
- have a thyroid problem
- plan to have surgery
- have low sodium levels in your blood
- receive electroconvulsive therapy (ECT)
- are pregnant or plan to become pregnant.
  - Taking chlordiazepoxide and amitriptyline hydrochloride tablets late in pregnancy may cause your baby to have symptoms of sedation (breathing problems, sluggishness, low muscle tone), and/or withdrawal symptoms (jitteriness, irritability, restlessness, shaking, excessive crying, feeding problems).
  - Tell your healthcare provider right away if you become pregnant or think you are pregnant during treatment with chlordiazepoxide and amitriptyline hydrochloride tablets.
  - There is a pregnancy registry for women who take chlordiazepoxide and amitriptyline hydrochloride tablets during pregnancy. The purpose of the registry is to collect information about the health of you and your baby. If you become pregnant during treatment with chlordiazepoxide and amitriptyline hydrochloride tablets, talk to your healthcare provider about registering with the National Pregnancy Registry for Psychiatric Medications. You can register by calling 1-866-961-2388 or visiting https://womansmentalhealth.org/pregnancyregistry/.
- are breastfeeding or plan to breastfeed. It is not known if chlordiazepoxide and amitriptyline hydrochloride pass into your breastmilk.
  - Talk to your healthcare provider about the best way to feed your baby if you take chlordiazepoxide and amitriptyline hydrochloride tablets.
  - Breastfeeding is not recommended during treatment with chlordiazepoxide and amitriptyline hydrochloride tablets.

Tell your healthcare provider about all the medicines you take, including prescription and over-the-counter medicines, vitamins, and herbal supplements.

Taking chlordiazepoxide and amitriptyline hydrochloride tablets with certain other medicines can cause side effects or affect how well chlordiazepoxide and amitriptyline hydrochloride tablets or the other medicines work.

Ask your healthcare provider if you are not sure if you are taking any of these medicines. Your healthcare provider can tell you if it is safe to take chlordiazepoxide and amitriptyline hydrochloride tablets with your other medicines.

Do not start or stop any other medicines during treatment with chlordiazepoxide and amitriptyline hydrochloride tablets without talking to your healthcare provider first. Stopping chlordiazepoxide and amitriptyline hydrochloride tablets suddenly may cause you to have serious side effects. See, “What are the possible side effects of chlordiazepoxide and amitriptyline hydrochloride tablets?”

Know the medicines you take. Keep a list of them to show to your healthcare provider and pharmacist when you get a new medicine.

How should I take chlordiazepoxide and amitriptyline hydrochloride tablets?

- Take chlordiazepoxide and amitriptyline hydrochloride tablets exactly as your healthcare provider tells you to take them.
- If you take too many chlordiazepoxide and amitriptyline hydrochloride tablets, call your healthcare provider or go to the nearest emergency room right away.

What are the possible side effects of chlordiazepoxide and amitriptyline hydrochloride tablets?

Chlordiazepoxide and amitriptyline hydrochloride tablets may cause serious side effects, including:

- See “What is the most important information I should know about chlordiazepoxide and amitriptyline hydrochloride tablets?”
- Chlordiazepoxide and amitriptyline hydrochloride tablets can make you sleepy or dizzy, and can slow your thinking and motor skills.
  - Do not drive, operate heavy machinery, or do other dangerous activities until you know how chlordiazepoxide and amitriptyline hydrochloride tablets affect you.
  - Do not drink alcohol or take other drugs that may make you sleepy or dizzy while taking chlordiazepoxide and amitriptyline hydrochloride tablets without first talking to your healthcare provider. When taken with alcohol or drugs that cause sleepiness or dizziness, chlordiazepoxide and amitriptyline hydrochloride tablets may make your sleepiness or dizziness much worse.
- Low sodium levels in your blood (hyponatremia). Low sodium levels in your blood that may be serious and may cause death, can happen during treatment with chlordiazepoxide and amitriptyline hydrochloride tablets. Elderly people and people who take certain medicines may be at a greater risk for developing low sodium levels in your blood. Signs and symptoms may include:
  - headache
  - difficulty concentrating
  - memory changes
  - confusion
  - weakness and unsteadiness on your feet which can lead to falls
  - In more severe or more sudden cases, signs and symptoms include:
    - seeing or hearing things that are not real (hallucinations)
    - fainting
    - seizures
    - coma
    - stopping breathing (respiratory arrest)

The most common side effects of chlordiazepoxide and amitriptyline hydrochloride tablets include:

- drowsiness
- dizziness
- blurred vision

- constipation
- dry mouth
- bloating

These are not all the possible side effects of chlordiazepoxide and amitriptyline hydrochloride tablets.

Call your doctor for medical advice about side effects. You may report side effects to FDA at 1-800-FDA-1088.

How should I store chlordiazepoxide and amitriptyline hydrochloride tablets?

- Store chlordiazepoxide and amitriptyline hydrochloride tablets at room temperature between 20° to 25°C (68° to 77°F).
- Store in a dry place.
- Keep chlordiazepoxide and amitriptyline hydrochloride tablets in a tightly closed, child-resistant container and out of the light.

Keep chlordiazepoxide and amitriptyline hydrochloride tablets and all medicines out of the reach of children.

General information about the safe and effective use of chlordiazepoxide and amitriptyline hydrochloride tablets.

Medicines are sometimes prescribed for purposes other than those listed in a Medication Guide. Do not use chlordiazepoxide and amitriptyline hydrochloride tablets for a condition for which they were not prescribed. Do not give chlordiazepoxide and amitriptyline hydrochloride tablets to other people, even if they have the same symptoms that you have. They may harm them. You can ask your pharmacist or healthcare provider for information about chlordiazepoxide and amitriptyline hydrochloride tablets that is written for health professionals.

What are the ingredients in chlordiazepoxide and amitriptyline hydrochloride tablets?

Active ingredients: chlordiazepoxide, amitriptyline hydrochloride

Inactive ingredients: colloidal silicon dioxide, croscarmellose sodium, hydroxypropyl cellulose, hypromellose, magnesium stearate, microcrystalline cellulose, polyethylene glycol, pregelatinized starch (corn), sodium lauryl sulfate and titanium dioxide. In addition, the
5 mg/12.5 mg tablets also contain D&C Yellow No. 10 Aluminum Lake, FD&C Blue No. 1 Aluminum Lake and FD&C Yellow No. 6 Aluminum Lake and the 10 mg/25 mg tablets also contain polydextrose and triacetin.

Manufactured for: Mylan Pharmaceuticals Inc., Morgantown, WV 26505 U.S.A.

For more information, call Mylan at 1-877-446-3679 (1-877-4-INFO-RX).

The brands listed are trademarks of their respective owners.

This Medication Guide has been approved by the U.S. Food and Drug Administration.

Manufactured for:
Mylan Pharmaceuticals Inc.
Morgantown, WV 26505 U.S.A.

Manufactured by:
ALPHAPHARM PTY LTD
15 Garnet Street
Carole Park QLD 4300
Australia

Revised: 7/2025

ALP:CDAM:R8mmh/ALP:MG:CDAM:R7m/ALP:MG:CDAM:R7mh

(3452/7)

PRINCIPAL DISPLAY PANEL – 5 mg/12.5 mg

NDC 0378-0211-01

Chlordiazepoxide
and
Amitriptyline HCl
Tablets, USP
CIV
5 mg/
12.5 mg*

Rx only 100 Tablets

*Each film-coated tablet contains
5 mg of chlordiazepoxide, USP and
14 mg of amitriptyline hydrochloride,
USP equivalent to 12.5 mg of
amitriptyline.

Dispense in a tight, light-resistant
container as defined in the USP
using a child-resistant closure.

Keep container tightly closed.

Keep this and all medication
out of the reach of children.

Store at 20° to 25°C (68° to 77°F).
[See USP Controlled Room
Temperature.]

Store in a dry place.

Usual Dosage: See
accompanying prescribing
information.

PHARMACIST: Dispense the
accompanying Medication
Guide to each patient.

Manufactured for:
Mylan Pharmaceuticals Inc.
Morgantown, WV 26505 U.S.A.

Made in Australia

3448/0

RALP0211A

PRINCIPAL DISPLAY PANEL – 10 mg/25 mg

NDC 0378-0277-01

Chlordiazepoxide
and
Amitriptyline HCl
Tablets, USP
CIV
10 mg/
25 mg*

Rx only 100 Tablets

*Each film-coated tablet contains
10 mg of chlordiazepoxide, USP and
27.98 mg of amitriptyline hydrochloride,
USP equivalent to 25 mg of
amitriptyline.

Dispense in a tight, light-resistant
container as defined in the USP
using a child-resistant closure.

Keep container tightly closed.

Keep this and all medication
out of the reach of children.

Store at 20° to 25°C (68° to 77°F).
[See USP Controlled Room
Temperature.]

Store in a dry place.

Usual Dosage: See
accompanying prescribing
information.

PHARMACIST: Dispense the
accompanying Medication
Guide to each patient.

Manufactured for:
Mylan Pharmaceuticals Inc.
Morgantown, WV 26505 U.S.A.

Made in Australia

3450/0

RALP0277A